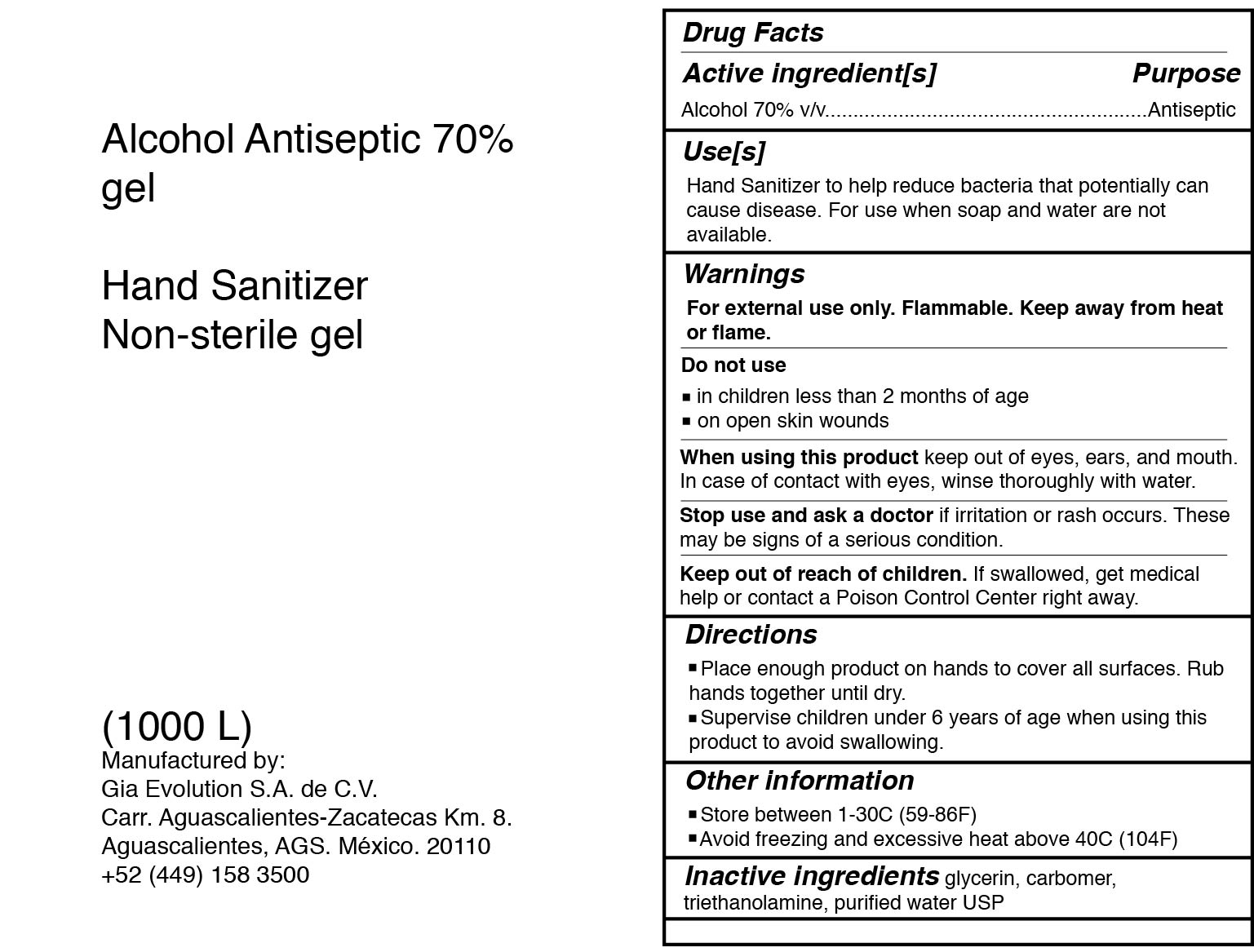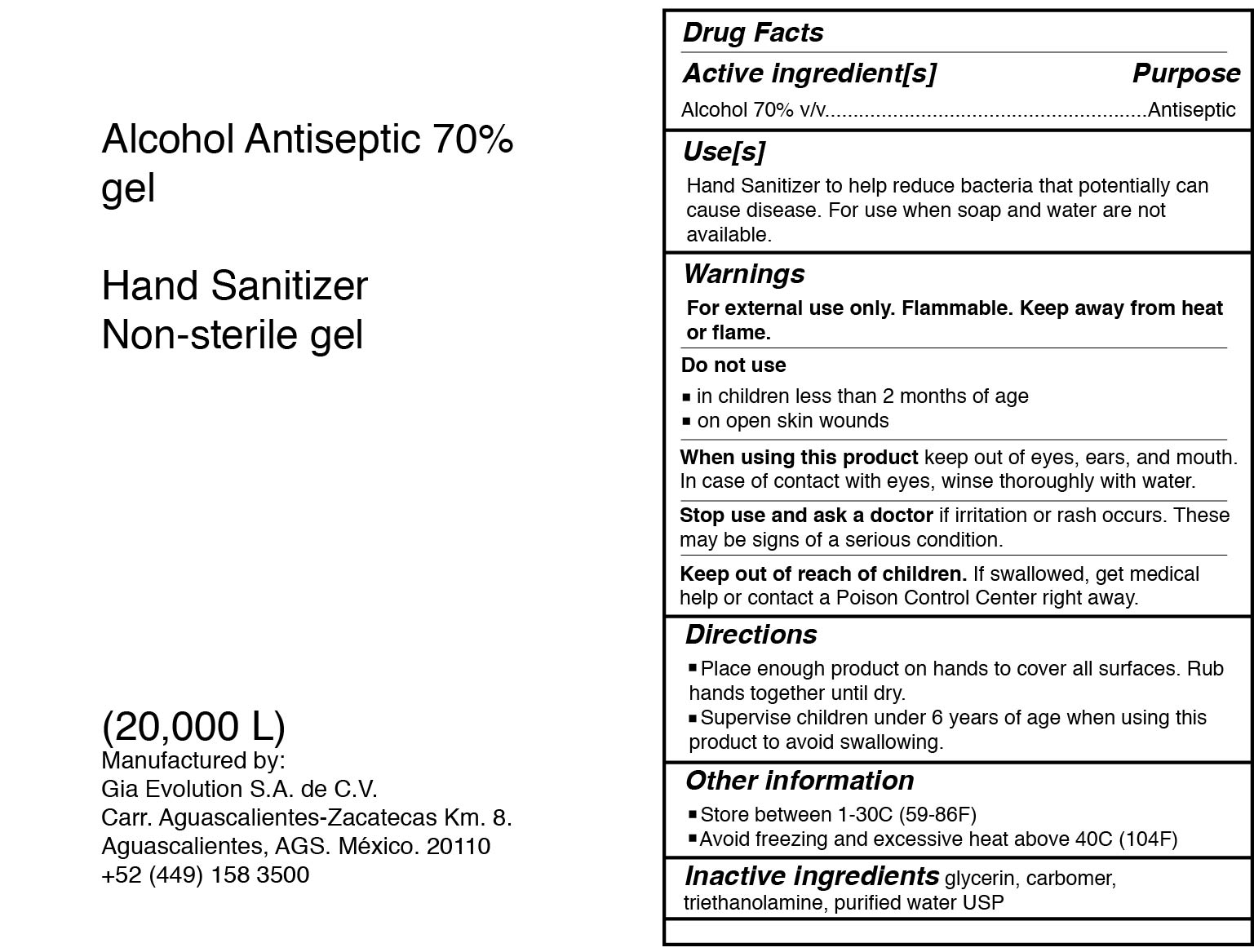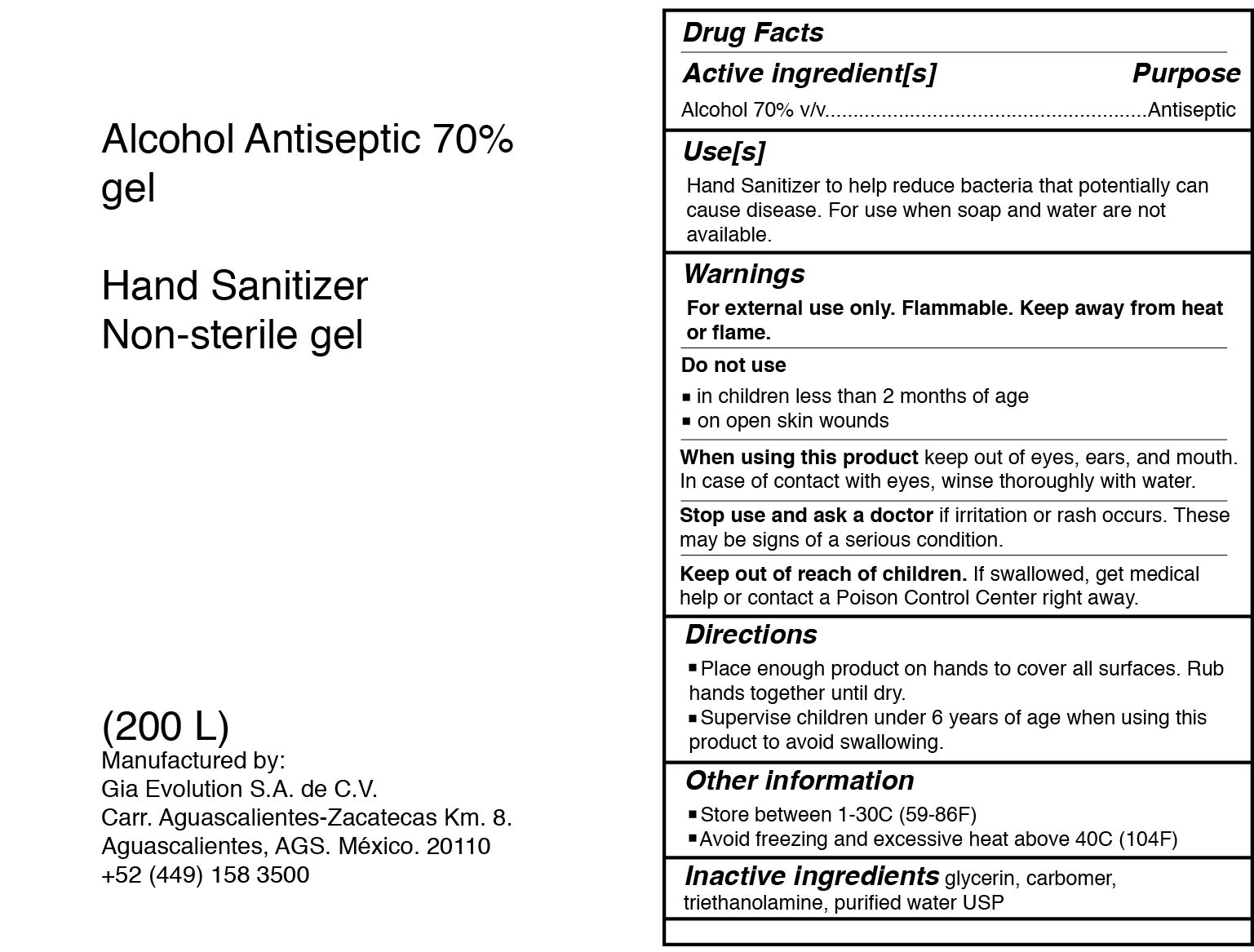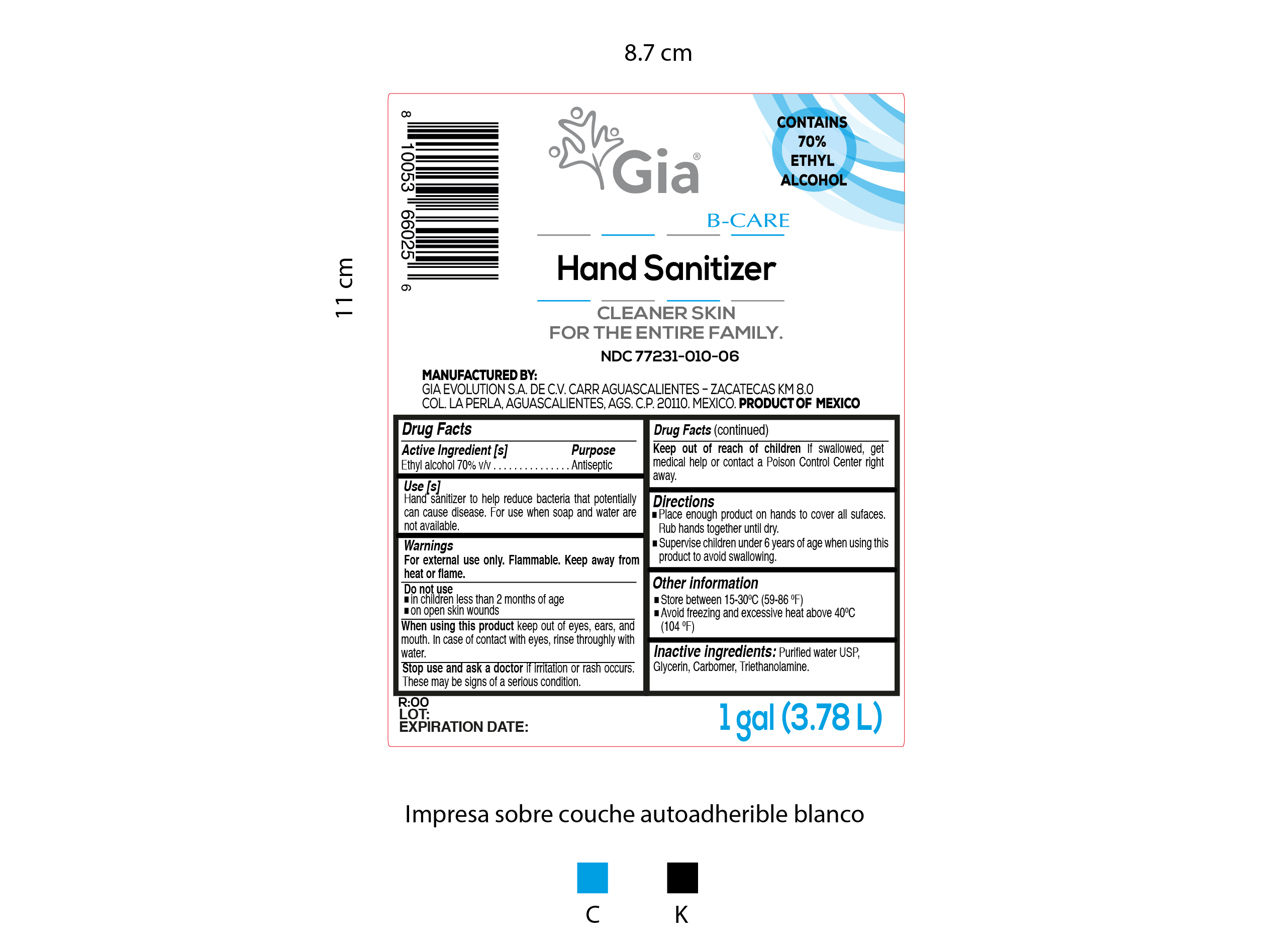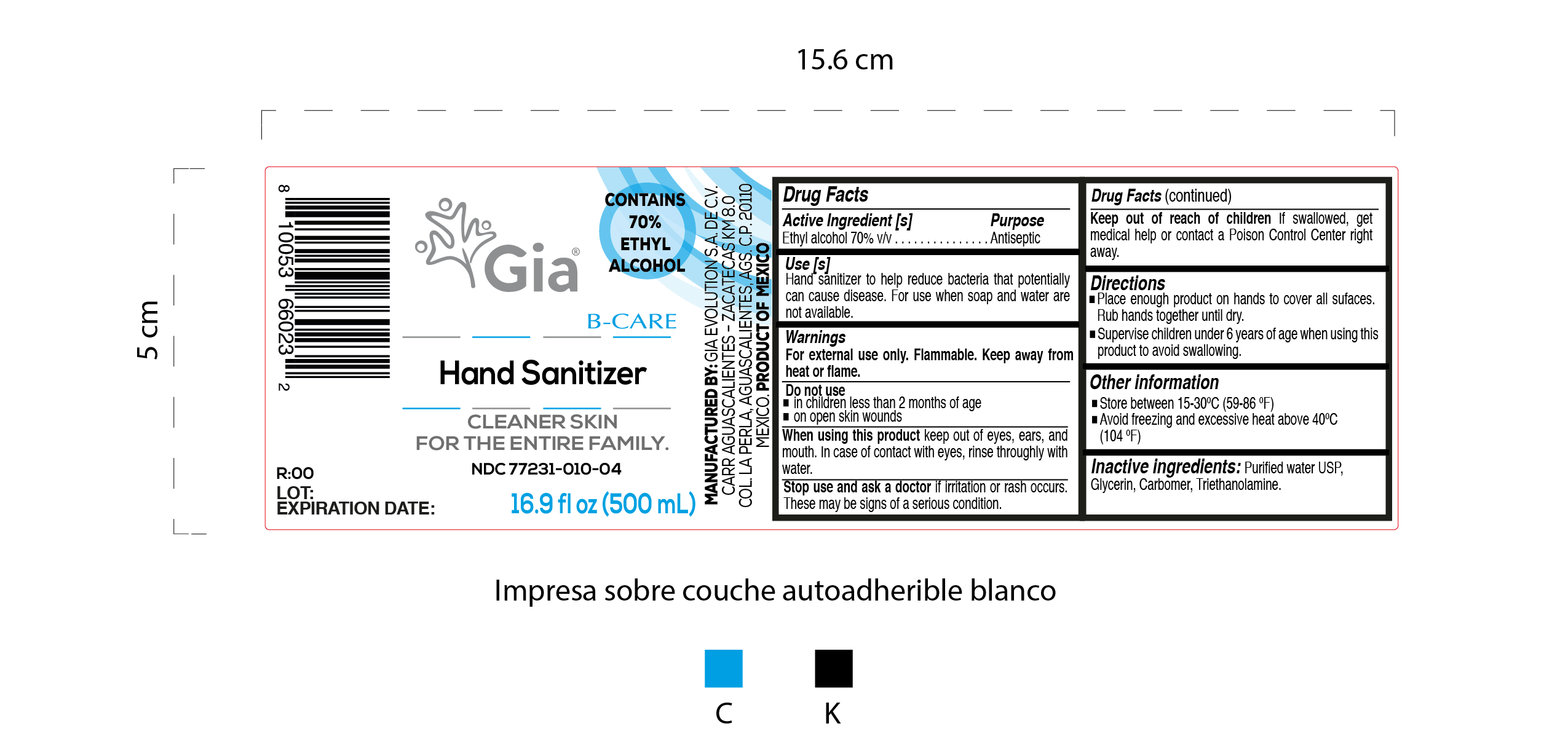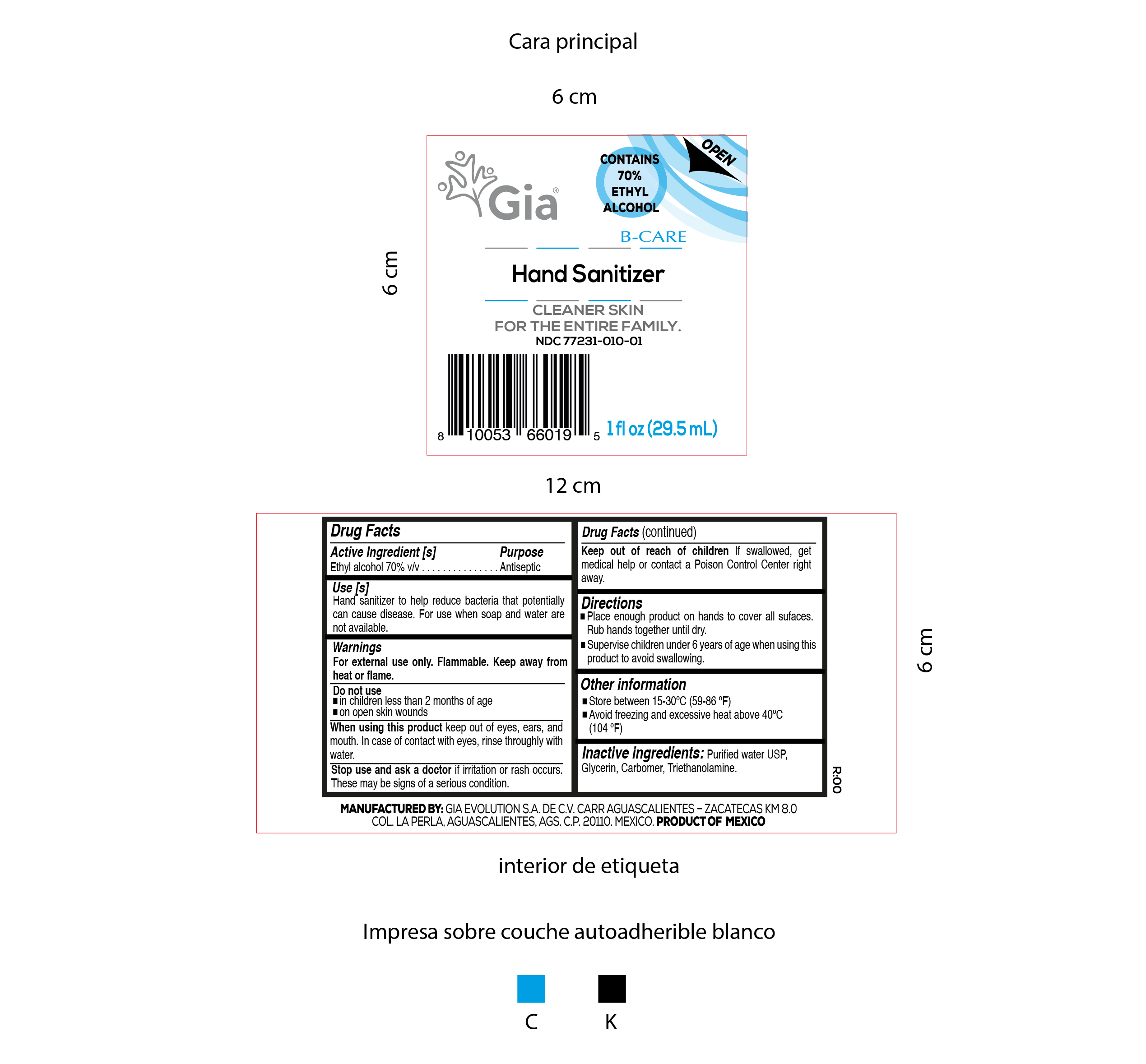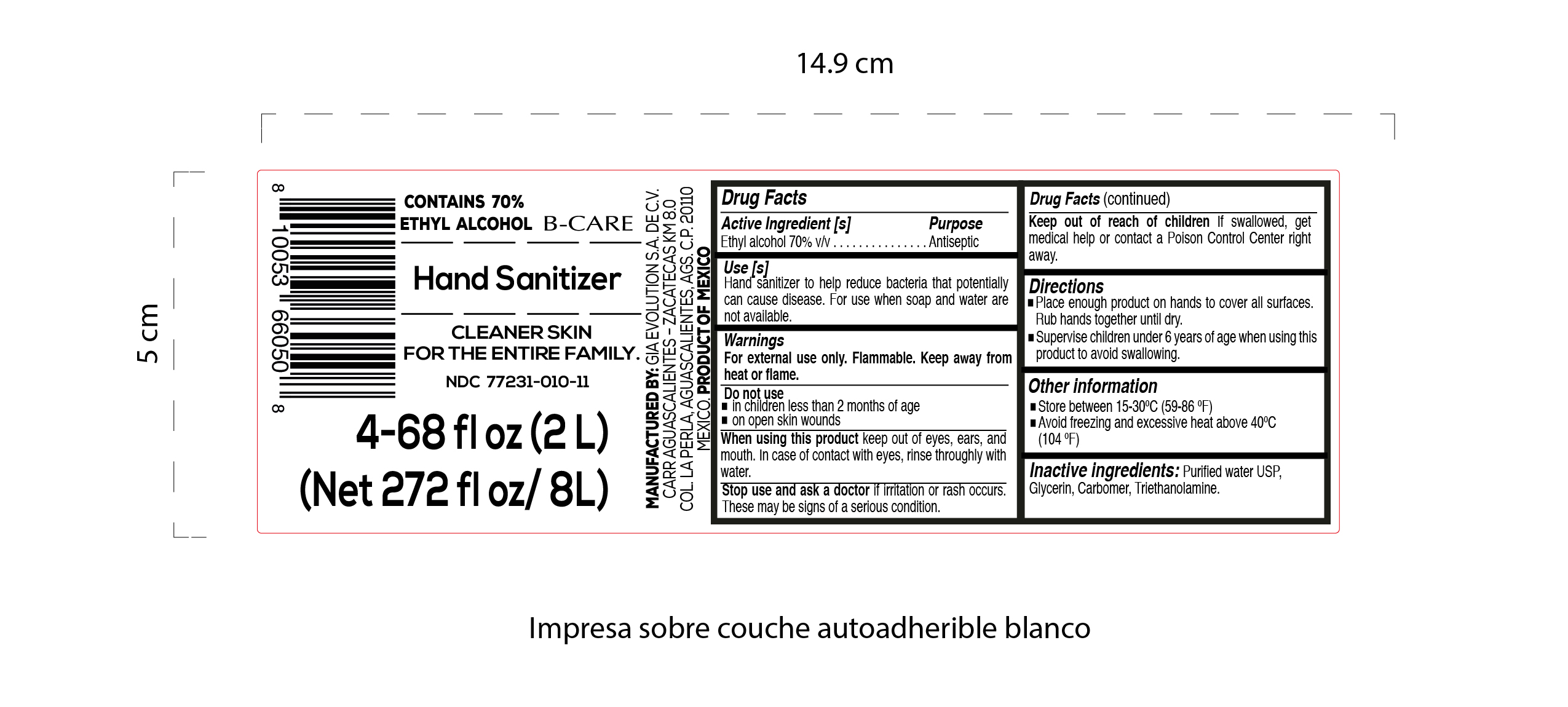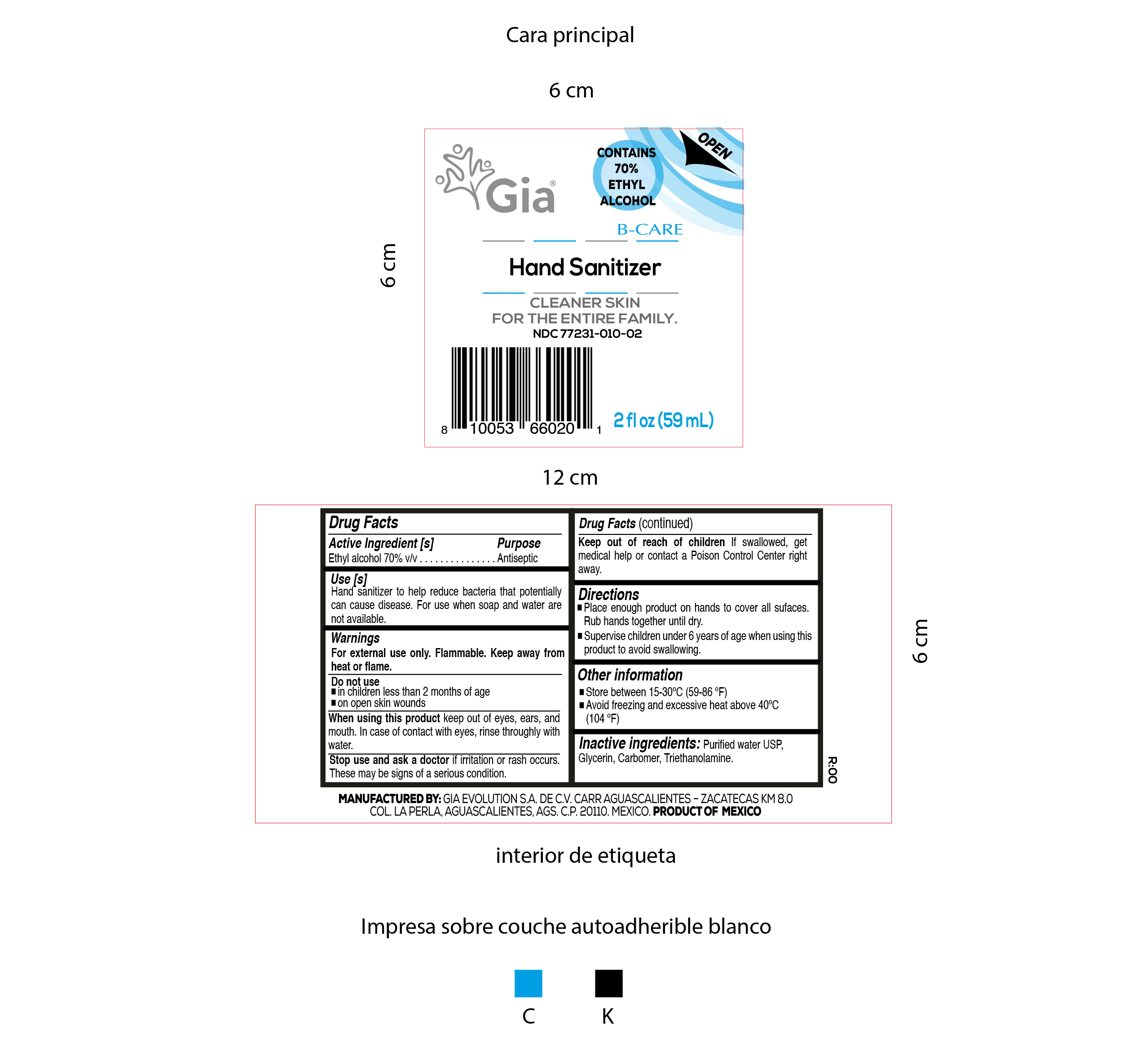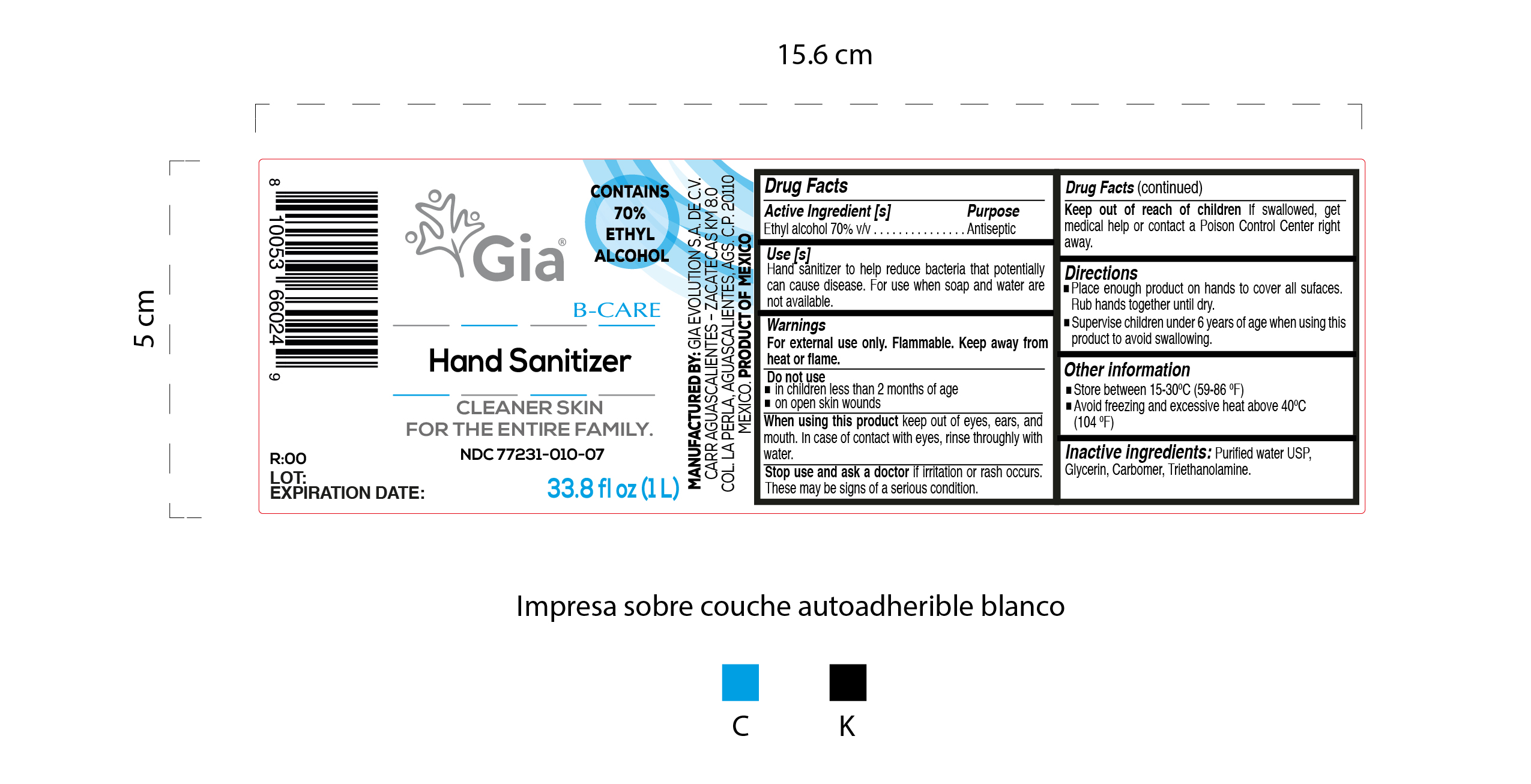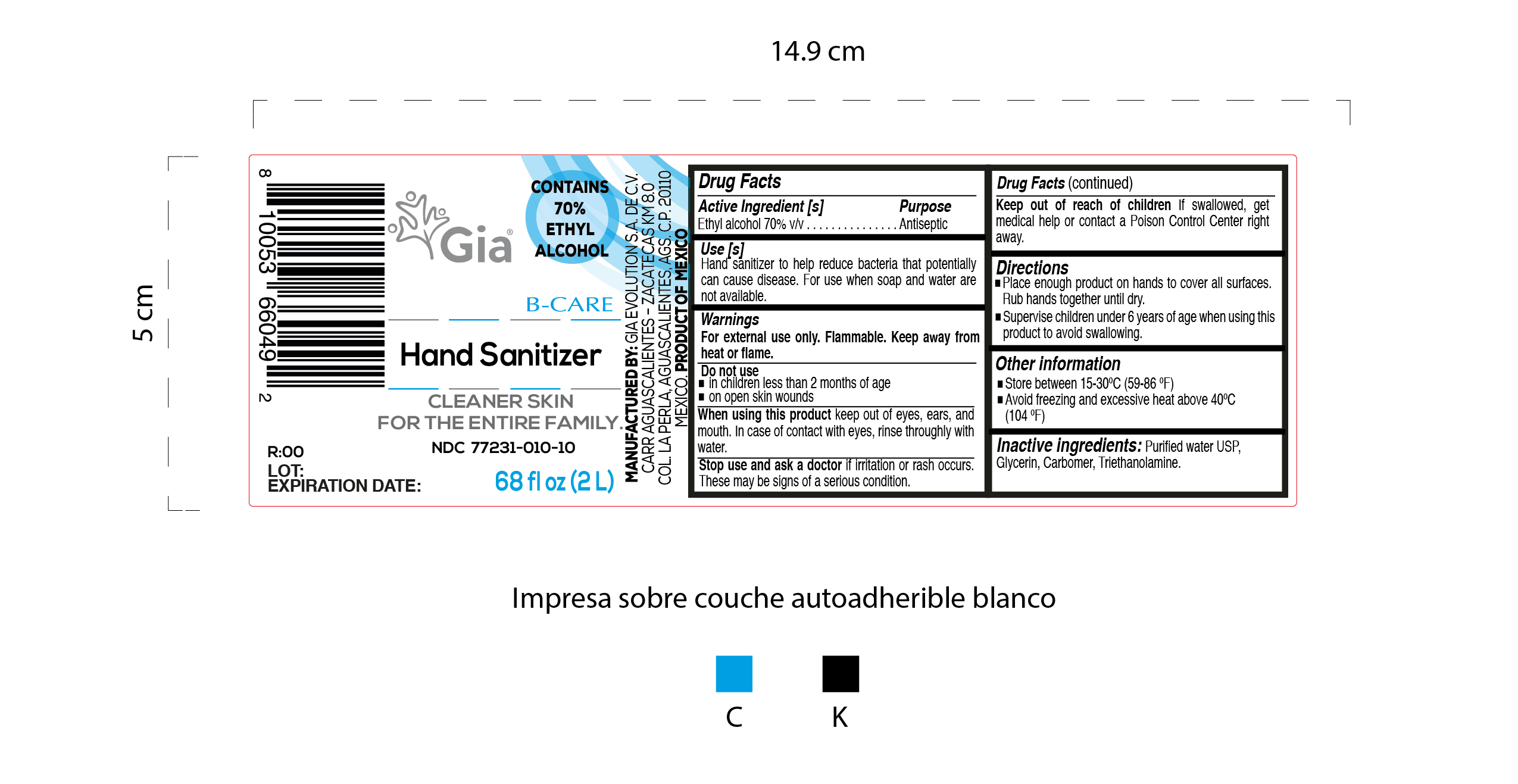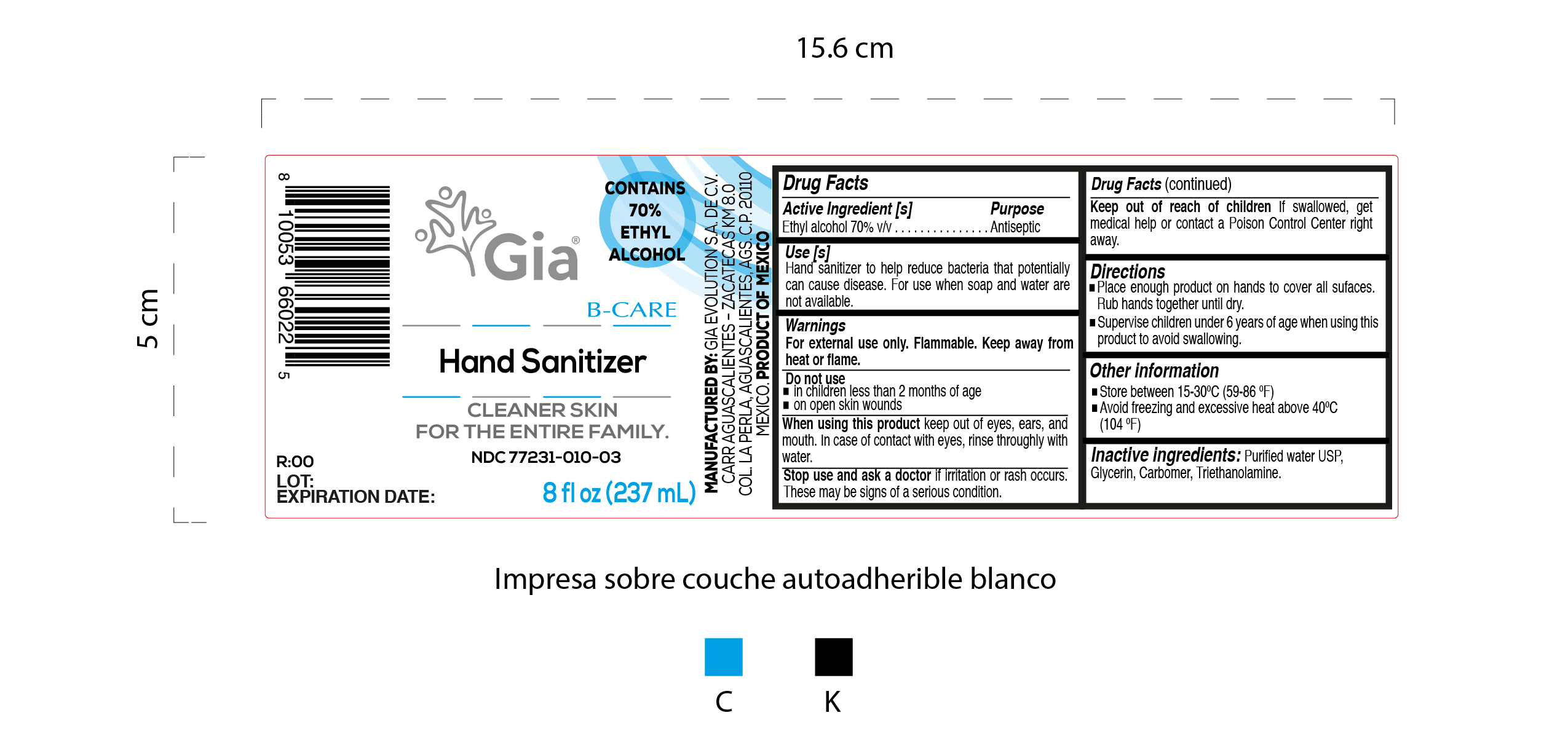 DRUG LABEL: Hand Sanitizer
NDC: 77231-010 | Form: GEL
Manufacturer: GIA EVOLUTION SA DE CV
Category: otc | Type: HUMAN OTC DRUG LABEL
Date: 20200702

ACTIVE INGREDIENTS: ALCOHOL 70 mL/100 mL
INACTIVE INGREDIENTS: CARBOMER 940 0.4 g/100 mL; GLYCERIN 1 mL/100 mL; TROLAMINE 0.35 g/100 mL; WATER

Active Ingredient(s)

Alcohol 70% v/v. Purpose: Antiseptic

Purpose

Antiseptic, Hand Sanitizer

Use

Hand Sanitizer to help reduce bacteria that potentially can cause disease. For use when soap and water are not available.

Warnings

For external use only. Flammable. Keep away from heat or flame

Do not use

- in children less than 2 months of age
- on open skin wounds

When using this product keep out of eyes, ears, and mouth. In case of contact with eyes, rinse eyes thoroughly with water.
Stop use and ask a doctor if irritation or rash occurs. These may be signs of a serious condition.
Keep out of reach of children. If swallowed, get medical help or contact a Poison Control Center right away.

Stop use and ask a doctor if irritation or rash occurs. These may be signs of a serious condition.

Keep out of reach of children. If swallowed, get medical help or contact a Poison Control Center right away.

Directions

- Place enough product on hands to cover all surfaces. Rub hands together until dry.
- Supervise children under 6 years of age when using this product to avoid swallowing.

Other information

- Store between 15-30C (59-86F)
- Avoid freezing and excessive heat above 40C (104F)

Inactive ingredients

purified water USP, glycerin, carbomer, triethanolamine.

Package Label - Principal Display Panel

29.5 mL NDC: 77231-010-01

59 mL NDC: 77231-010-02

237 mL NDC: 77231-010-03

500 mL NDC: 77231-010-04

946 mL NDC: 77231-010-05

3785 mL NDC: 77231-010-06

200000 mL NDC: 77231-010-08

1000000 mL NDC: 77231-010-07

20000000 mL NDC: 77231-010-09

2000 mL NDC: 77231-010-10

8000 mL NDC: 77231-010-11